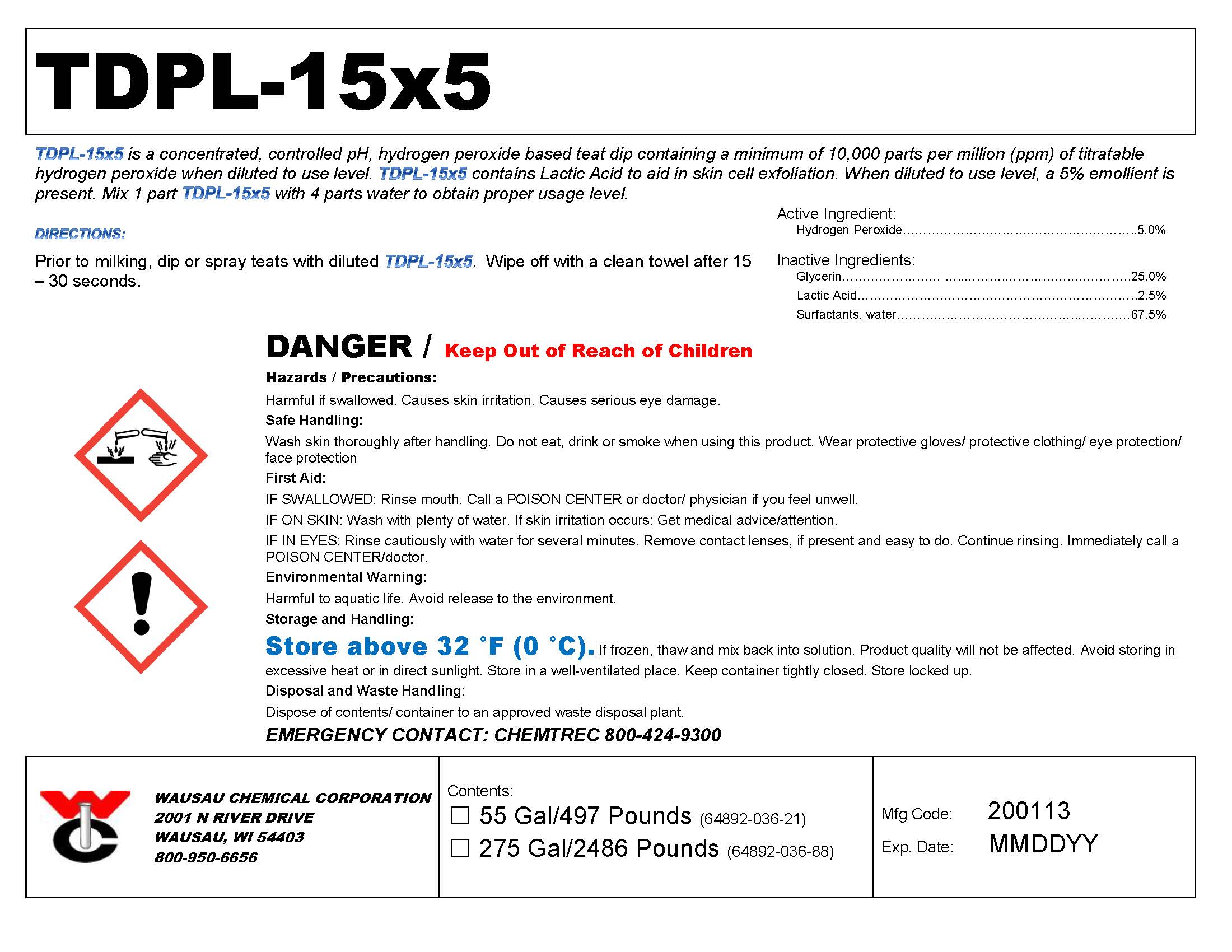 DRUG LABEL: TDPL-15x5
NDC: 64892-036 | Form: SOLUTION
Manufacturer: Wausau Chemical
Category: animal | Type: OTC ANIMAL DRUG LABEL
Date: 20200114

ACTIVE INGREDIENTS: HYDROGEN PEROXIDE 50 g/1 L

TDPL-15x5
Concentrated Hydrogen Peroxide Teat Dip with Lactic Acid

DISPOSAL AND WASTE HANDLING

Dispose of contents/container to an approved waste disposal plant.

ENVIRONMENTAL WARNING

Harmful to aquatic life. Avoid release to the environment.

GENERAL PRECAUTIONS

DANGER / Keep Out of Reach of Children

Harmful if swallowed. Causes skin irritation. Causes serious eye damage.

First Aid:

IF SWALLOWED: Rinse mouth. Call a POISON CENTER or doctor/ physician if you feel unwell.

IF ON SKIN: Wash with plenty of water. If skin irritation occurs: Get medical advice/attention.

IF IN EYES: Rinse cautiously with water for several minutes. Remove contact lenses, if present and easy to do. Continue rinsing. Immediately call a POISON CENTER/doctor.

SAFE HANDLING WARNING

Wash skin thoroughly after handling. Do not eat, drink or smoke when using this product. Wear protective gloves/ protective clothing/ eye protection/ face protection.

STORAGE AND HANDLING

Store above 32 °F (0 °C). If frozen, thaw and mix back into solution. Product quality will not be affected.

Avoid storing in excessive heat or in direct sunlight. Store in a well-ventilated place. Keep container tightly closed. Store locked up.

DIRECTIONS:

Mix 1 part TDPL-15x5 with 4 parts water to obtain proper usage level.

Prior to milking, dip or spray teats with diluted TDPL-15x5. Wipe off with a clean towel after 15 – 30 seconds.

Active Ingredient:
Hydrogen Peroxide………………………………………………………………5.0%

Wausau Chemical Corporation

2001 N River Drive

Wausau, WI 54403

800-950-6656